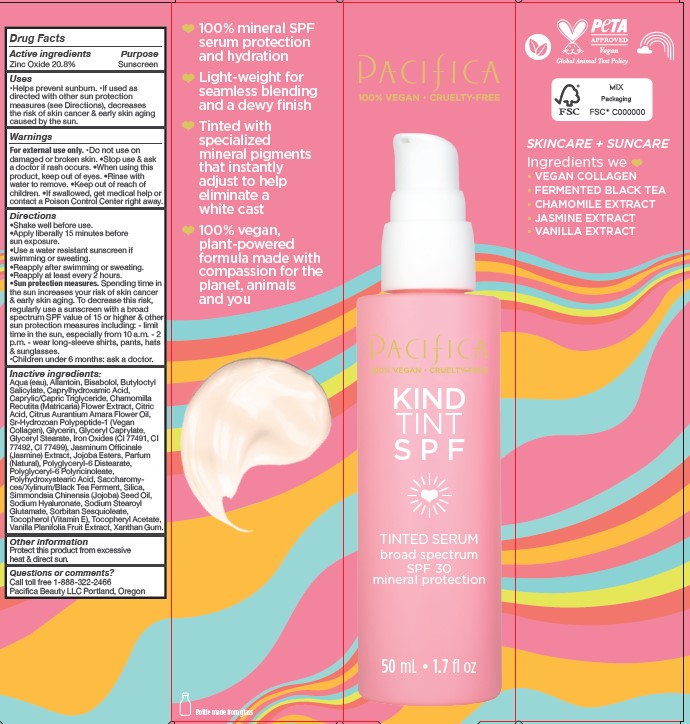 DRUG LABEL: Kind Tint SPF 30
NDC: 61197-218 | Form: LIQUID
Manufacturer: Pacifica Beauty, LLC
Category: otc | Type: HUMAN OTC DRUG LABEL
Date: 20250103

ACTIVE INGREDIENTS: ZINC OXIDE 20.8 g/100 mL
INACTIVE INGREDIENTS: MEDIUM-CHAIN TRIGLYCERIDES; GLYCERIN; BUTYLOCTYL SALICYLATE; CITRIC ACID MONOHYDRATE; SORBITAN SESQUIOLEATE; VANILLA PLANIFOLIA WHOLE; XANTHAN GUM; POLYHYDROXYSTEARIC ACID (2300 MW); HYALURONATE SODIUM; SODIUM STEAROYL GLUTAMATE; TOCOPHEROL; HYDROGENATED JOJOBA OIL, RANDOMIZED; POLYGLYCERYL-6 POLYRICINOLEATE; ALPHA-TOCOPHEROL ACETATE; FERRIC OXIDE YELLOW; ALLANTOIN; GLYCERYL CAPRYLATE; GLYCERYL STEARATE SE; FERRIC OXIDE RED; CITRUS AURANTIUM FLOWER OIL; WATER; .ALPHA.-BISABOLOL, (+)-; CAPRYLHYDROXAMIC ACID; JASMINUM OFFICINALE WHOLE; FERROSOFERRIC OXIDE; HYDROLYZED JOJOBA ESTERS (POTASSIUM SALTS); MATRICARIA CHAMOMILLA FLOWERING TOP OIL

Kind Tint SPF 30

Active ingredients Purpose

Zinc Oxide 20.8% Sunscreen

Uses

Helps prevent sunburn. If used as directed with other sun protection measures (see Directions), decreases the risk of skin cancer & early skin aging caused by the sun.

INDICATIONS AND USAGE

If used as directed with other sun protection measures (see Directions), decreases the risk of skin cancer & early skin aging caused by the sun.

Warnings

For external use only. Do not use on damaged or broken skin. Stop use & ask a doctor if rash occurs. When using this product, keep out of eyes. Rinse with water to remove. Keep out of reach of children. If swallowed, get medical help or contact a Poison Control Center right away.

Keep out of reach of children.

Directions

Shake well before use. Apply liberally 15 minutes before sun exposure. Use a water resistant sunscreen if swimming or sweating. Reapply after swimming or sweating. Reapply at least every 2 hours. Sun protection measures. Spending time in the sun increases your risk of skin cancer & early skin aging. To decrease this risk, regularly use a sunscreen with a broad spectrum SPF value of 15 or higher & other sun protection measures including: - limit time in the sun, especially from 10 a.m. - 2 p.m. - wear long-sleeve shirts, pants, hats & sunglasses. Children under 6 months: ask a doctor.

Inactive ingredients:

Aqua (eau), Allantoin, Bisabolol, Butyloctyl Salicylate, Caprylhydroxamic Acid, Caprylic/Capric Triglyceride, Chamomilla Recutita (Matricaria) Flower Extract, Citric Acid, Citrus Aurantium Amara Flower Oil, Sr-Hydrozoan Polypeptide-1 (Vegan Collagen), Glycerin, Glyceryl Caprylate, Glyceryl Stearate, Iron Oxides (CI 77491, CI 77492, CI 77499), Jasminum Officinale (Jasmine) Extract, Jojoba Esters, Parfum (Natural), Polyglyceryl-6 Distearate, Polyglyceryl-6 Polyricinoleate, Polyhydroxystearic Acid, Saccharomyces/Xylinum/Black Tea Ferment, Silica, Simmondsia Chinensis (Jojoba) Seed Oil, Sodium Hyaluronate, Sodium Stearoyl Glutamate, Sorbitan Sesquioleate, Tocopherol (Vitamin E), Tocopheryl Acetate, Vanilla Planifolia Fruit Extract, Xanthan Gum.

Other information

Protect this product from excessive heat & direct sun.

Questions or comments?

Call toll free 1-888-322-2466
Pacifica Beauty LLC Portland, Oregon